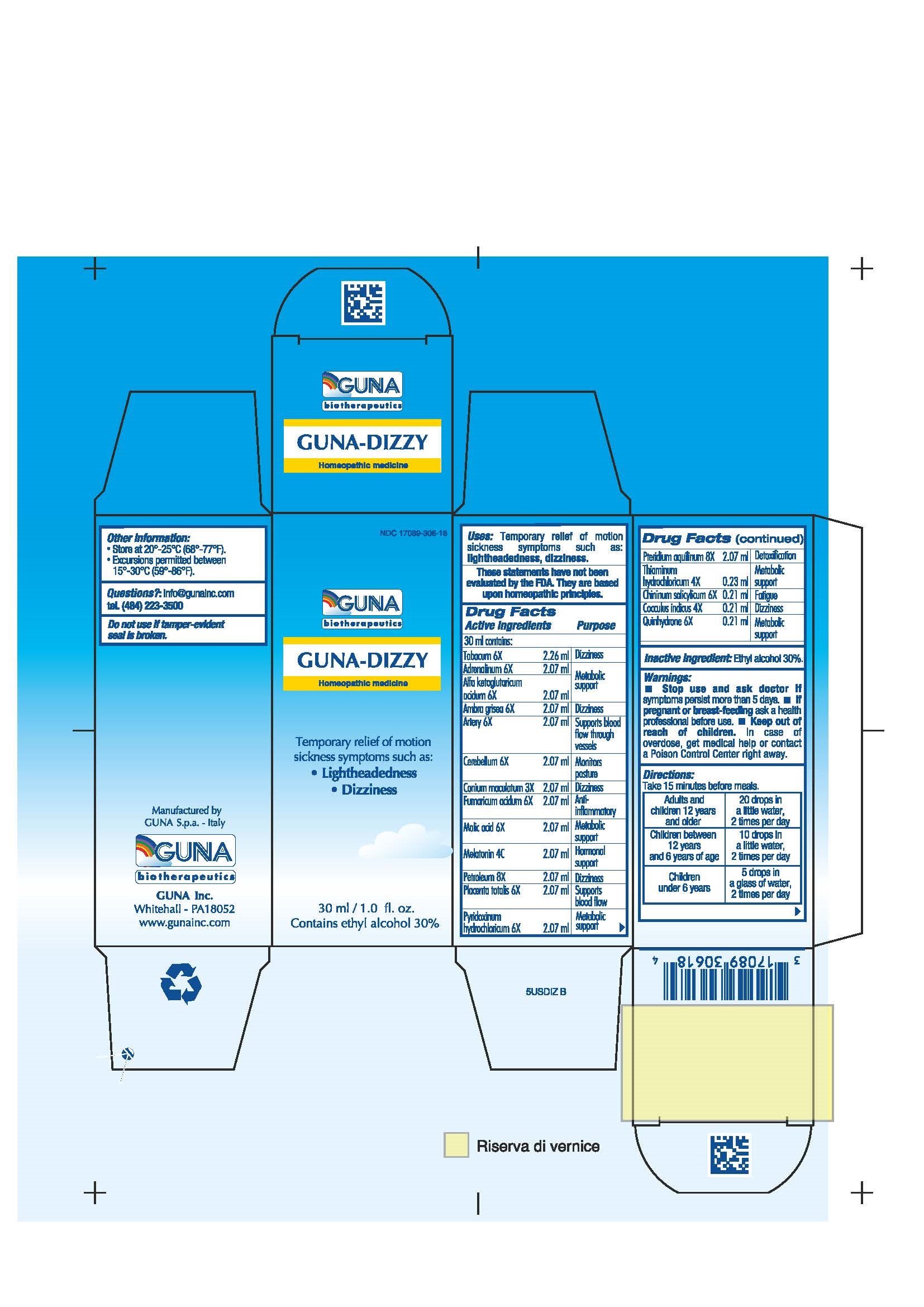 DRUG LABEL: GUNA-DIZZY
NDC: 17089-306 | Form: SOLUTION/ DROPS
Manufacturer: Guna spa
Category: homeopathic | Type: HUMAN OTC DRUG LABEL
Date: 20181221

ACTIVE INGREDIENTS: EPINEPHRINE 6 [hp_X]/30 mL; .ALPHA.-KETOGLUTARIC ACID 6 [hp_X]/30 mL; AMBERGRIS 6 [hp_X]/30 mL; SUS SCROFA ARTERY 6 [hp_X]/30 mL; SUS SCROFA CEREBELLUM 6 [hp_X]/30 mL; QUININE SALICYLATE 6 [hp_X]/30 mL; ANAMIRTA COCCULUS SEED 4 [hp_X]/30 mL; CONIUM MACULATUM FLOWERING TOP 3 [hp_X]/30 mL; FUMARIC ACID 6 [hp_X]/30 mL; MALIC ACID 6 [hp_X]/30 mL; MELATONIN 4 [hp_C]/30 mL; MINERAL OIL 8 [hp_X]/30 mL; SUS SCROFA PLACENTA 6 [hp_X]/30 mL; PTERIDIUM AQUILINUM ROOT 8 [hp_X]/30 mL; PYRIDOXINE HYDROCHLORIDE 6 [hp_X]/30 mL; QUINHYDRONE 6 [hp_X]/30 mL; TOBACCO LEAF 6 [hp_X]/30 mL; THIAMINE HYDROCHLORIDE 4 [hp_X]/30 mL
INACTIVE INGREDIENTS: ALCOHOL 9 mL/30 mL

GUNA-DIZZY

ACTIVE INGREDIENTS/PURPOSE

ADRENALINUM 6X METABOLIC SUPPORT
ALFA KETOGLUTARICUM ACIDUM 6X METABOLIC SUPPORT
AMBRA GIRSEA 6X DIZZINESS
ARTERY 6X SUPPORTS BLOOD FLOW THROUGH VESSELS
CEREBELLUM 6X MONITORS POSTURE
CHININUM SALICYLICUM 6X FATIGUE
COCCULUS INDICUS 4X DIZZINESS
CONIUM MACULATUM 3X DIZZINESS
FUMARICUM ACIDUM 6X ANTI-INFLAMMATORY
MALIC ACID 6X METABOLIC SUPPORT
MELATONIN 4C HORMONAL SUPPORT
PETROLEUM 8X DIZZINESS
PLACENTA TOTALIS 6X SUPPORTS BLOOD FLOW
PTERIDIUM AQUILINUM 8X DETOXIFICATION
PYRIDOXINUM HYDROCHLORICUM 6X METABOLIC SUPPORT
QUINHYDRONE 6X METABOLIC SUPPORT
TABACUM 6X DIZZINESS
THIAMINUM HYDROCHLORICUM 4X METABOLIC SUPPORT

USES

Temporary relief of motion sickness symptoms such as:

- Lightheadedness
- Dizziness

WARNINGS

Stop use and ask doctor if symptoms persist more than 5 days.
If pregnant or breast-feeding ask a health professional before use.
Keep out of reach of children. In case of overdose, get medical help or contact a Poison Control Center right away.
Contains ethyl alcohol 30%

PREGNANCY

If pregnant or breast-feeding ask a doctor before use

WARNINGS

Keep out of reach of children

DIRECTIONS

Adults and children 12 years and older 20 drops in a little water, 2 times per day
Children between 12 years and 6 years of age 10 drops in a little water, 2 times per day
Children under 6 years 5 drops in a glass of water, 2 times per day

QUESTIONS

Questions?: info@gunainc.com
tel. (484) 223-3500

INDICATIONS AND USAGE

Take 15 minutes before meals

Inactive Ingredient: Ethyl alcohol 30%,